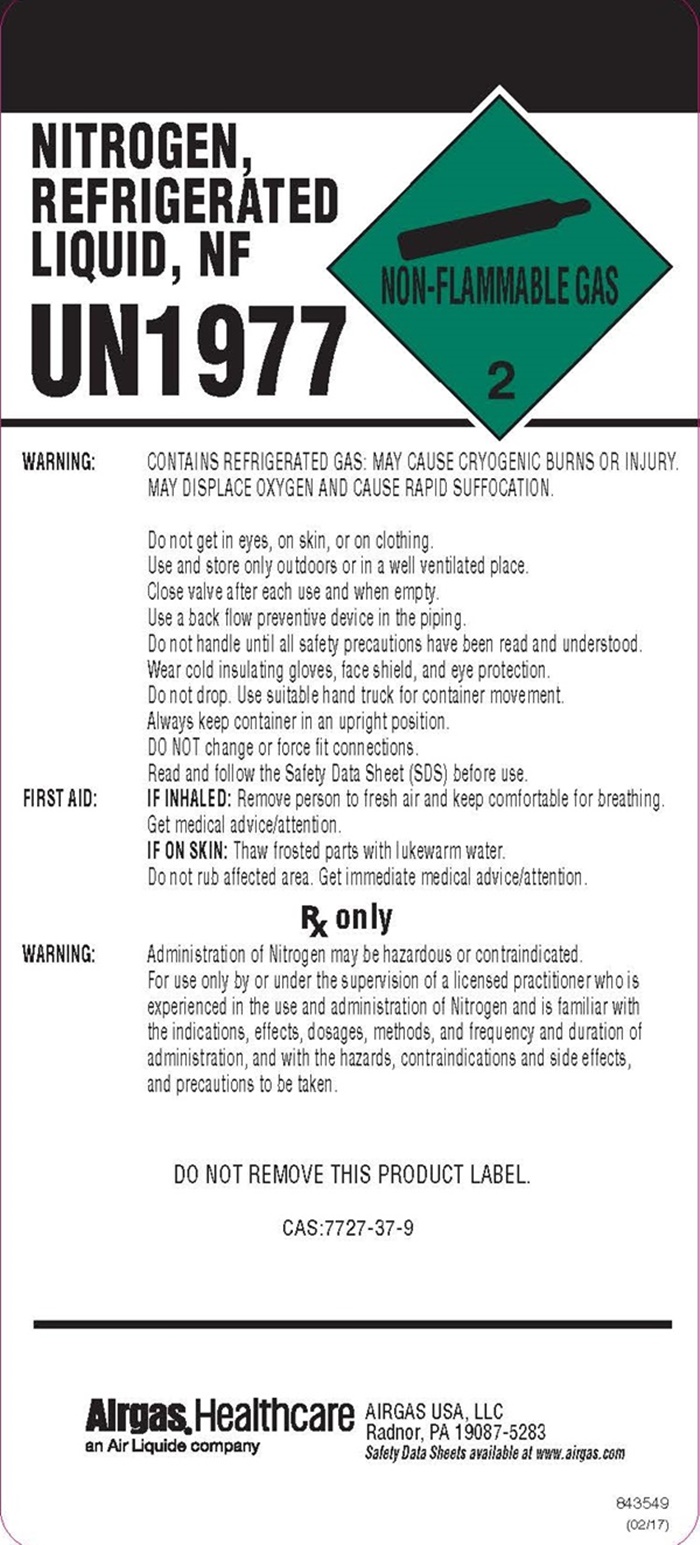 DRUG LABEL: Nitrogen, Refrigerated
NDC: 11054-006 | Form: LIQUID
Manufacturer: Airgas Usa, LLC
Category: prescription | Type: HUMAN PRESCRIPTION DRUG LABEL
Date: 20260115

ACTIVE INGREDIENTS: NITROGEN 992 mL/1 L

Nitrogen, Refrigerated Liquid - 006

Nitrogen Refrigerated product label

NITROGEN, REFRIGERATED LIQUID NF

UN1977

NON-FLAMMABLE GAS 2

WARNING: CONTAINS REFRIGERATED GAS: MAY CAUSE CRYOGENIC BURNS OR INJURY. MAY DISPLACE OXYGEN AND CAUSE RAPID SUFFOCATION.

Do not get in eyes, on skin, or on clothing.

Use and store only outdoors or in a well ventilated place.

Close valve after each use and when empty.

Use a back flow preventive device in the piping.

Do not handle until all safety precautions have been read and understood.

Wear cold insulating gloves/face shield/eye protection.

Do not drop. Use suitable hand truck for container movement.

Always keep container in an upright position.

DO NOT change or force fit connections.

Read and follow the Safety Data Sheet (SDS) before use.

FIRST AID: IF INHALED: Remove person to fresh air and keep comfortable for breathing.

Get medical advice/attention.

IF ON SKIN: Thaw frosted parts with lukewarm water.

Do not rub affected area. Get immediate medical advice/attention.

Rx only

WARNING: Administration of Nitrogen may be hazardous or contraindicated.

For use only by or under the supervision of a licensed practitioner who is experienced in the use and administration of Nitrogen and is familiar with the indications, effects, dosages, methods, and frequency, and duration of administration, and with the hazards, contraindications and side effects and the precautions to be taken.

DO NOT REMOVE THIS PRODUCT LABEL
CAS: 7727-37-9

Airgas® Healthcare

an Air Liquide company

AIRGAS USA, LLC

Radnor, PA 19087-5283

Safety Data Sheets available at www.airgas.com

843549
(02/17)